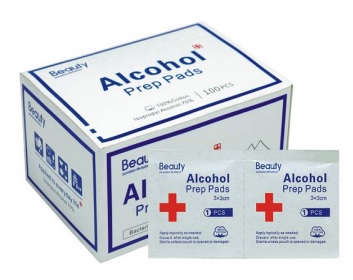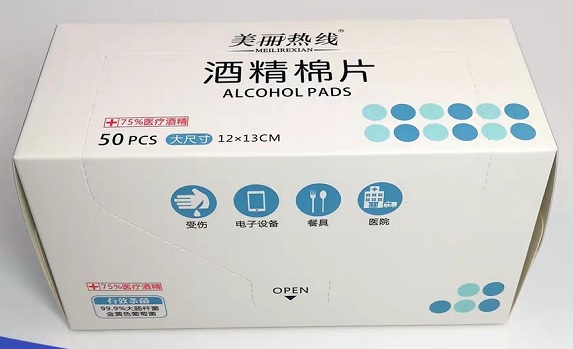 DRUG LABEL: Alcohol prep pad
NDC: 75111-101 | Form: LIQUID
Manufacturer: Enping Jiaxin Daily Necessities Co., Ltd.
Category: otc | Type: HUMAN OTC DRUG LABEL
Date: 20200410

ACTIVE INGREDIENTS: ALCOHOL 0.75 mL/1 mL
INACTIVE INGREDIENTS: WATER

Alcohol prep pad(75111-101)

Alcohol prep pad

Active Ingredient(s)

Alcohol 75% v/v. Purpose: Antiseptic

Purpose

Antiseptic

Use

Wipe the surface of the object to sterilize and disinfect

Warnings

For external use only. Flammable. Keep away from heat or flame

Do not use

- in children less than 2 months of age
- on open skin wounds

When using this product keep out of eyes, ears, and mouth. In case of contact with eyes, rinse eyes thoroughly with water.
Stop use and ask a doctor if irritation or rash occurs. These may be signs of a serious condition.
Keep out of reach of children. If swallowed, get medical help or contact a Poison Control Center right away.

Stop use and ask a doctor if irritation or rash occurs. These may be signs of a serious condition.

Keep out of reach of children. If swallowed, get medical help or contact a Poison Control Center right away.

Directions

- Wipe the surface of the object
- Supervise children under 6 years of age when using this product to avoid swallowing.

Other information

- Store between 15-30C (59-86F)
- Avoid freezing and excessive heat above 40C (104F)

Inactive ingredients

purified water USP

Package Label - Principal Display Panel

25 PCS NDC: 75111-101-01

50 PCS NDC: 75111-101-01

100 PCS NDC: 75111-101-01